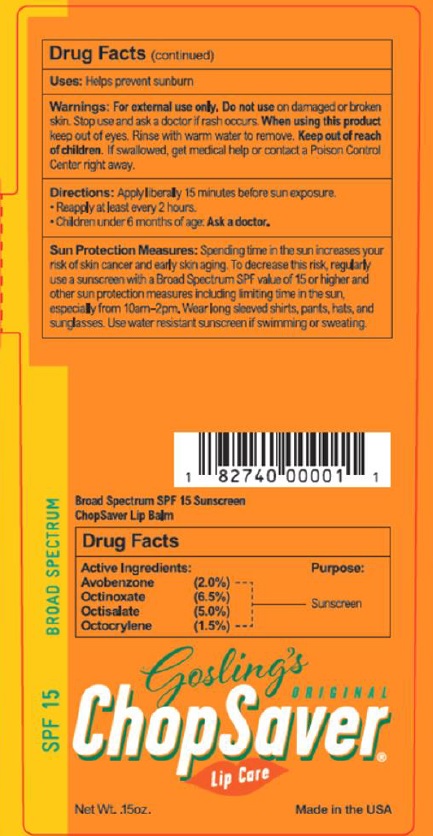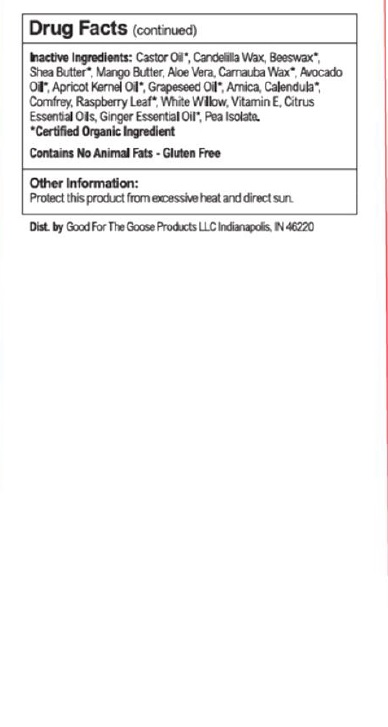 DRUG LABEL: ChopSaver SPF 15 Lip Care
NDC: 83724-001 | Form: LIPSTICK
Manufacturer: Good For The Goose Products, LLC dba ChopSaver
Category: otc | Type: HUMAN OTC DRUG LABEL
Date: 20231005

ACTIVE INGREDIENTS: AVOBENZONE 2 g/100 g; OCTINOXATE 6.5 g/100 g; OCTISALATE 5 g/100 g; OCTOCRYLENE 1.5 g/100 g
INACTIVE INGREDIENTS: CASTOR OIL; CANDELILLA WAX; YELLOW WAX; SUNFLOWER OIL; SHEA BUTTER; MANGIFERA INDICA SEED BUTTER; CARNAUBA WAX; AVOCADO OIL; APRICOT KERNEL OIL; GRAPE SEED OIL; LEMON OIL, DISTILLED; .ALPHA.-TOCOPHEROL; GRAPEFRUIT OIL; ORANGE OIL, DISTILLED; LIME OIL, DISTILLED; GINGER OIL; ARNICA MONTANA WHOLE; CALENDULA OFFICINALIS FLOWER; RUBUS IDAEUS LEAF; COMFREY LEAF; ALOE VERA LEAF; WILLOW BARK; PEA PROTEIN

Active ingredient Purpose

AVOBENZONE 2.0% Sunscreen
OCTINOXATE 6.5% Sunscreen
OCTISALATE 5.0% Sunscreen
OCTOCRYLENE 1.5% Sunscreen

Uses

Helps prevent sunburn

Warnings

For external use only.

Do not use ondamaged or broken skin.

Stop use and ask a doctorif rash occurs.

When using this productkeep out of eyes. Rinse with warm water to remove.

Keep out of reach of children. If swallowed, get medical help or contact a Poison Control Center right away.

Directions

Apply liberally 15 minutes before sun exposure.
• Reapply at least every 2 hours.
• Children under 6 months of age: Ask a doctor.

Sun Protection Measures: Spending time in the sun increases your risk of skin cancer and early skin aging. To decrease this risk, regularly use a sunscreen with a Broad Spectrum SPF value of 15 or higher and other sun protection measures including limiting time in the sun, especially from 10am-2pm. Wear long sleeved shirts, pants, hats, and sunglasses. Use water resistant sunscreen if swimming or sweating.

Inactive Ingredients

Castor Oil*, Candelilla Wax, Beeswax*, Shea Butter*, Mango Butter, Aloe Vera, Carnauba Wax*, Avocado Oil*, Apricot Kernel Oil*, Grapeseed Oil*, Arnica, Calendula*, Comfrey, Raspberry Leaf*, White Willow, Vitamin E, Citrus Essential Oils, Ginger Essential Oil*,Pea Isolate

*Certified Organic Ingredient - No animal fats - Gluten free

Other information

Protect this product from excessive heat and direct sun.